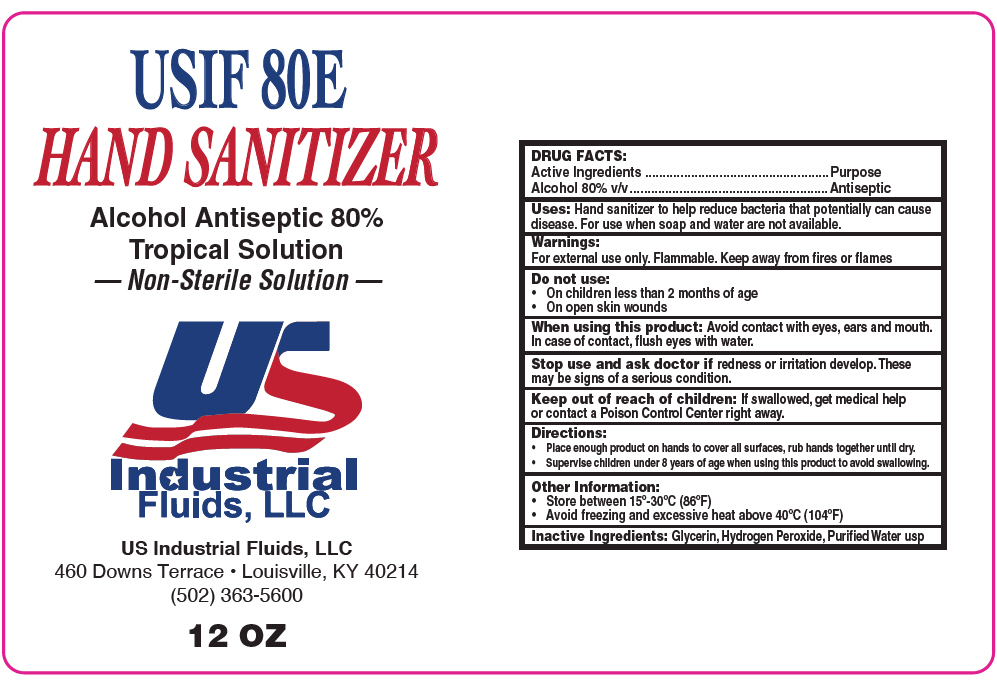 DRUG LABEL: USIF 80E Hand Sanitizer
NDC: 77439-080 | Form: LIQUID
Manufacturer: US Industrial Fluids,LLC
Category: otc | Type: HUMAN OTC DRUG LABEL
Date: 20200519

ACTIVE INGREDIENTS: Alcohol 80 mL/100 mL
INACTIVE INGREDIENTS: WATER; GLYCERIN; HYDROGEN PEROXIDE

USIF 80E Hand Sanitizer

DRUG FACTS:

Active Ingredients

Alcohol 80% v/v

Purpose

Antiseptic

Uses

Hand sanitizer to help reduce bacteria that potentially can cause disease. For use when soap and water are not available.

Warnings

For external use only. Flammable. Keep away from fires or flames

Do not use

- On children less than 2 months of age
- On open skin wounds

When using this product

Avoid contact with eyes, ears and mouth. In case of contact, flush eyes with water.

Stop use and ask doctor if redness or irritation develop. These may be signs of a serious condition.

Keep out of reach of children

If swallowed, get medical help or contact a Poison Control Center right away.

Directions

- Place enough product on hands to cover all surfaces, rub hands together until dry.
- Supervise children under 8 years of age when using this product to avoid swallowing.

Other Information

- Store between 15°-30°C (86°F)
- Avoid freezing and excessive heat above 40°C (104°F)

Inactive Ingredients

Glycerin, Hydrogen Peroxide, Purified Water usp

PRINCIPAL DISPLAY PANEL - 12 OZ Bottle Label

USIF 80E
HAND SANITIZER

Alcohol Antiseptic 80%
Tropical Solution
— Non-Sterile Solution —

US Industrial Fluids, LLC
460 Downs Terrace • Louisville, KY 40214
(502) 363-5600

12 OZ